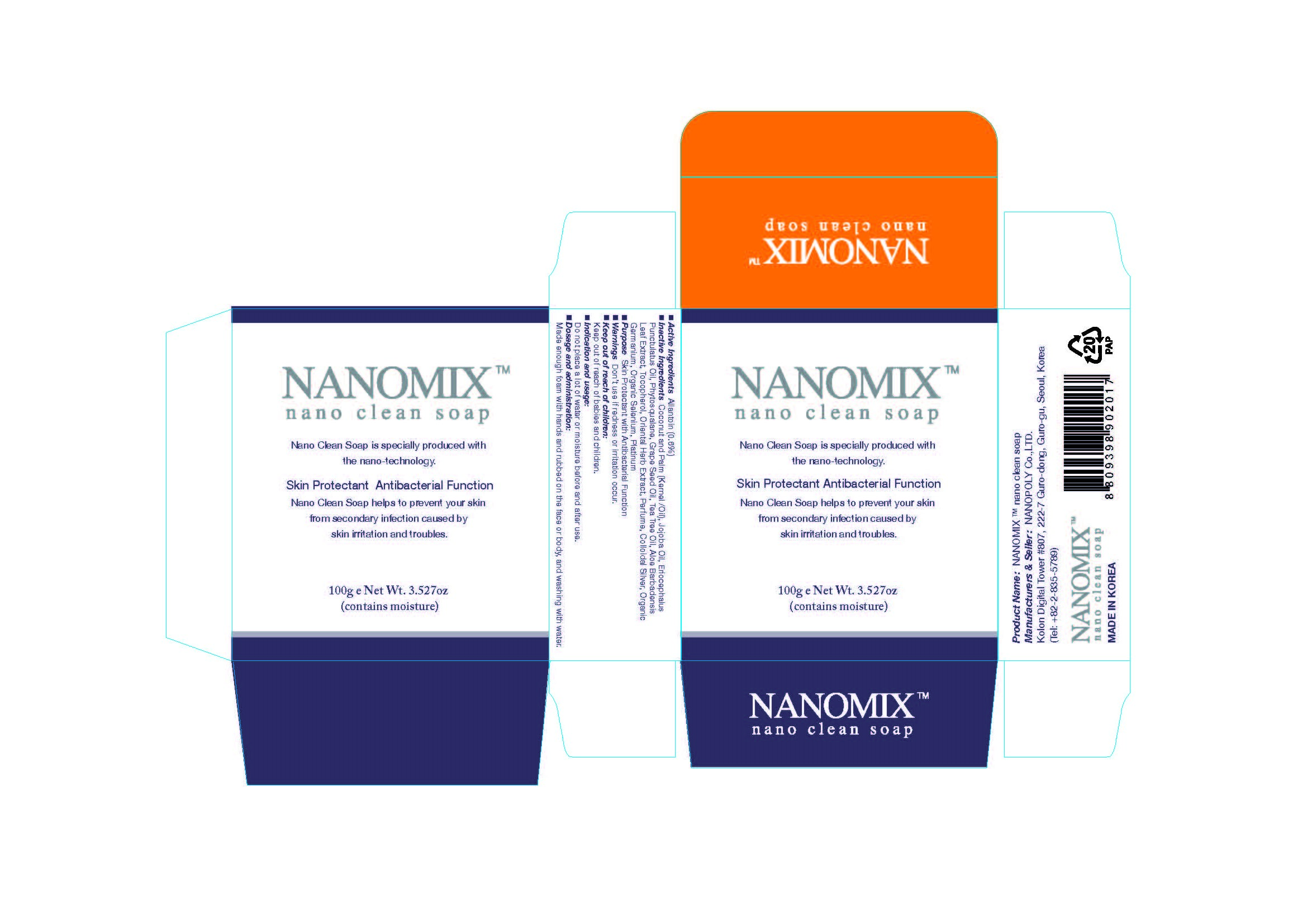 DRUG LABEL: NANOMIX NANO CLEAN
NDC: 54170-120 | Form: SOAP
Manufacturer: NANOPOLY CO., LTD.
Category: otc | Type: HUMAN OTC DRUG LABEL
Date: 20130830

ACTIVE INGREDIENTS: Allantoin 0.6 g/100 g
INACTIVE INGREDIENTS: GRAPE SEED OIL

ACTIVE INGREDIENT

Active Ingredients: Allantoin 0.6%

INACTIVE INGREDIENT

Inactive Ingredients:
Coconut and Palm (Kernel /Oil), Jojoba Oil, Eriocephalus Punctulatus Oil, Phytosqualane, Grape Seed Oil, Tea Tree Oil, Aloe Barbadensis Leaf Extract, Tocopherol, Oriental Herb Extract, Perfume, Colloidal Silver, Organic Germanium, Organic Selenium, Platinum

PURPOSE

Purpose: Skin Protectant with Antibacterial Function

WARNINGS

Don't use if redness or irritation occur.

KEEP OUT OF REACH OF CHILDREN

Keep out of reach of babies and children.

INDICATIONS AND USAGE

Indication and usage:
Do not place a lot of water or moisture before and after use.

DOSAGE AND ADMINISTRATION

Made enough foam with hands and rubbed on the face or body, and washing with water.